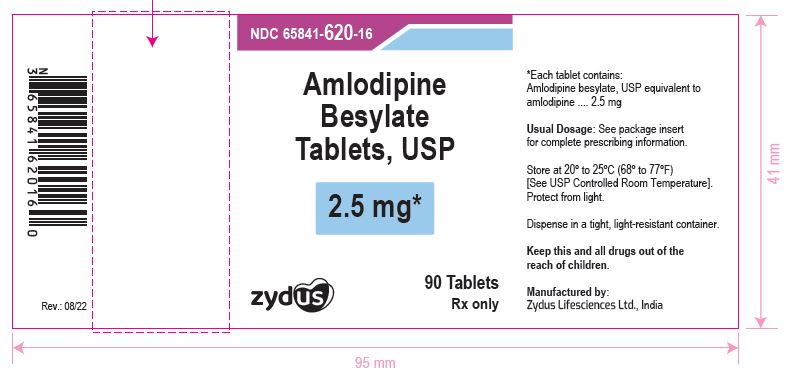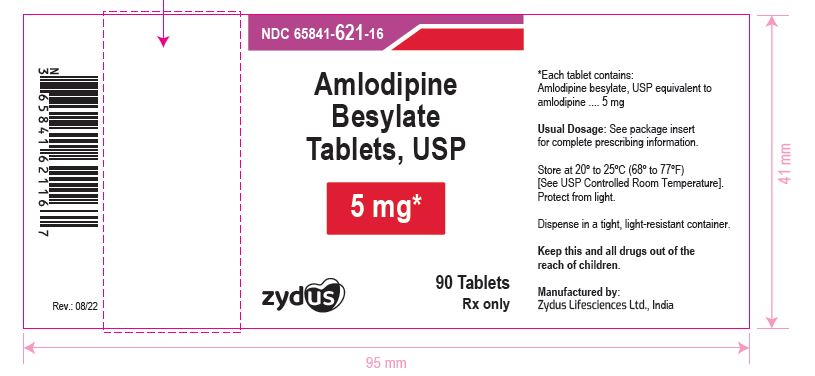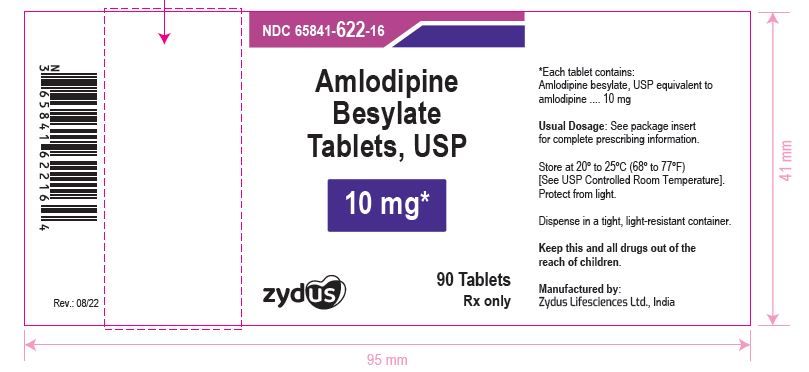 DRUG LABEL: Amlodipine Besylate
NDC: 65841-620 | Form: TABLET
Manufacturer: Zydus Lifesciences Limited
Category: prescription | Type: HUMAN PRESCRIPTION DRUG LABEL
Date: 20241125

ACTIVE INGREDIENTS: AMLODIPINE BESYLATE 2.5 mg/1 1
INACTIVE INGREDIENTS: MAGNESIUM STEARATE; SODIUM STARCH GLYCOLATE TYPE A POTATO; SILICON DIOXIDE; CELLULOSE, MICROCRYSTALLINE

AMLODIPINE Besylate Tablets

PACKAGE LABEL.PRINCIPAL DISPLAY PANEL

NDC 65841-620-16 in bottle of 90 tablets

Amlodipine Besylate Tablets USP, 2.5 mg

Rx only

90 tablets

NDC 65841-621-16 in bottle of 90 tablets

Amlodipine Besylate Tablets USP, 5 mg

Rx only

90 tablets

NDC 65841-622-16 in bottle of 90 tablets

Amlodipine Besylate Tablets USP, 10 mg

Rx only

90 tablets